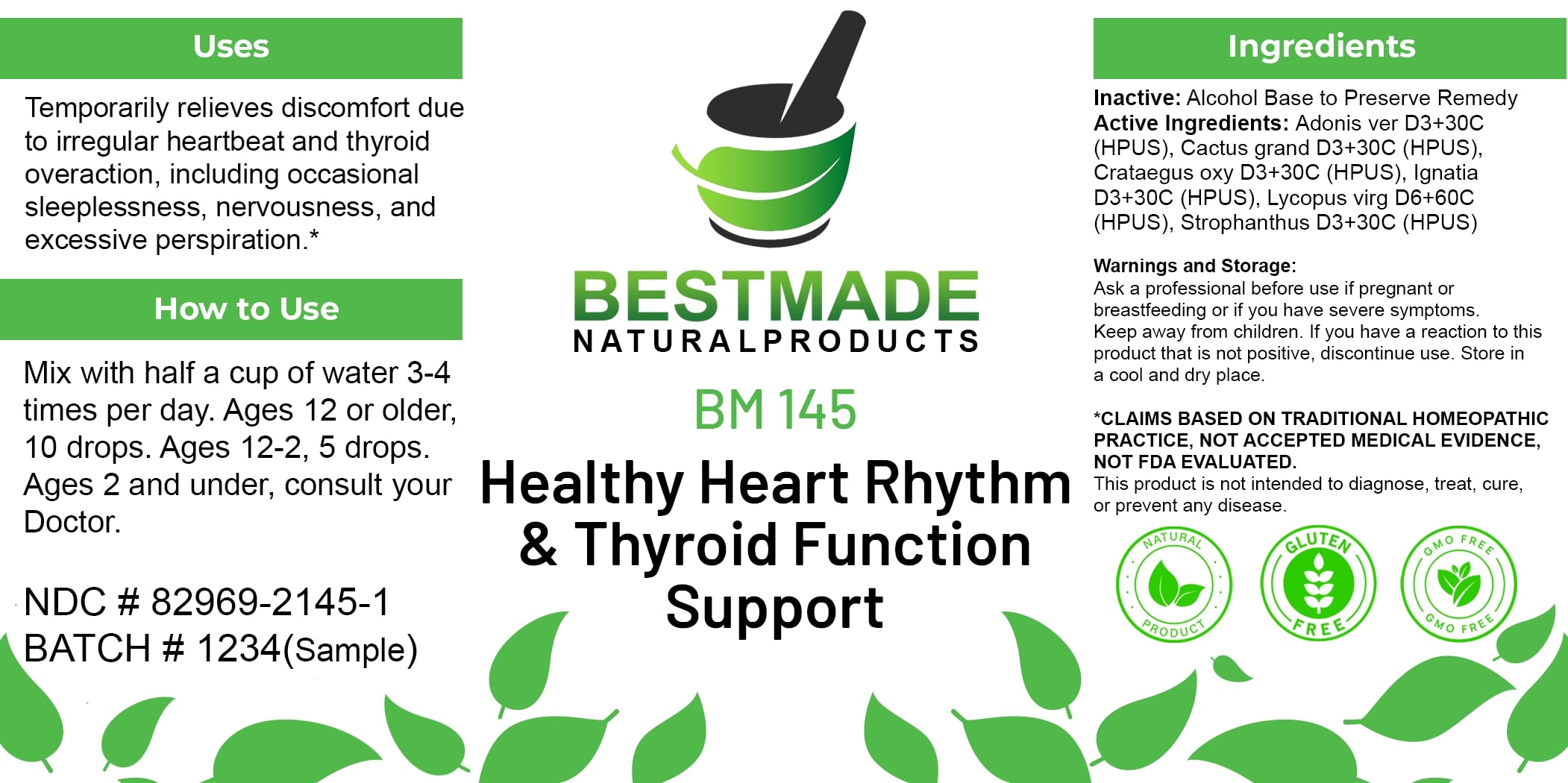 DRUG LABEL: Bestmade Natural Products BM145
NDC: 82969-2145 | Form: LIQUID
Manufacturer: Bestmade Natural Products
Category: homeopathic | Type: HUMAN OTC DRUG LABEL
Date: 20250325

ACTIVE INGREDIENTS: STROPHANTHUS HISPIDUS SEED 30 [hp_C]/30 [hp_C]; SELENICEREUS GRANDIFLORUS STEM 30 [hp_C]/30 [hp_C]; CRATAEGUS LAEVIGATA WHOLE 30 [hp_C]/30 [hp_C]; STRYCHNOS IGNATII SEED 30 [hp_C]/30 [hp_C]; LYCOPUS VIRGINICUS WHOLE 30 [hp_C]/30 [hp_C]; ADONIS VERNALIS WHOLE 30 [hp_C]/30 [hp_C]
INACTIVE INGREDIENTS: ALCOHOL 30 [hp_C]/30 [hp_C]

DOSAGE AND ADMINISTRATION

How to Use

Mix with half a cup of water 3-4 times per day. Ages 12 or older, 10 drops. Ages 12-2, 5 drops. Ages 2 and under, consult your Doctor.

Uses

Temporarily relieves discomfort due to irregular heartbeat and thyroid overaction, including occasional sleeplessness, nervousness, and excessive perspiration.*

*CLAIMS BASED ON TRADITIONAL HOMEOPATHIC PRACTICE, NOT ACCEPTED MEDICAL EVIDENCE, NOT FDA EVALUATED.

This product is not intended to diagnose, treat, cure, or prevent any disease.

INACTIVE INGREDIENT

Ingredients

Inactive: Alcohol Base to Preserve Remedy

ACTIVE INGREDIENT

Active Ingredients: Adonis ver D3+30C (HPUS), Cactus grand D3+30C (HPUS), Crataegus oxy D3+30C (HPUS), Ignatia D3+30C (HPUS), Lycopus virg D6+60C (HPUS), Strophanthus D3+30C (HPUS)

KEEP OUT OF REACH OF CHILDREN

Warnings and Storage:

Ask a professional before use if pregnant or breastfeeding or if you have severe symptoms. Keep away from children. If you have a reaction to this product that is not positive, discontinue use. Store in a cool and dry place.

Uses

Temporarily relieves discomfort due to irregular heartbeat and thyroid overaction, including occasional sleeplessness, nervousness, and excessive perspiration.*

*CLAIMS BASED ON TRADITIONAL HOMEOPATHIC PRACTICE, NOT ACCEPTED MEDICAL EVIDENCE, NOT FDA EVALUATED.

This product is not intended to diagnose, treat, cure, or prevent any disease.

Warnings and Storage:

Ask a professional before use if pregnant or breastfeeding or if you have severe symptoms. Keep away from children. If you have a reaction to this product that is not positive, discontinue use. Store in a cool and dry place.

*CLAIMS BASED ON TRADITIONAL HOMEOPATHIC PRACTICE, NOT ACCEPTED MEDICAL EVIDENCE, NOT FDA EVALUATED. This product is not intended to diagnose, treat, cure, or prevent any disease.

Entire Package Label